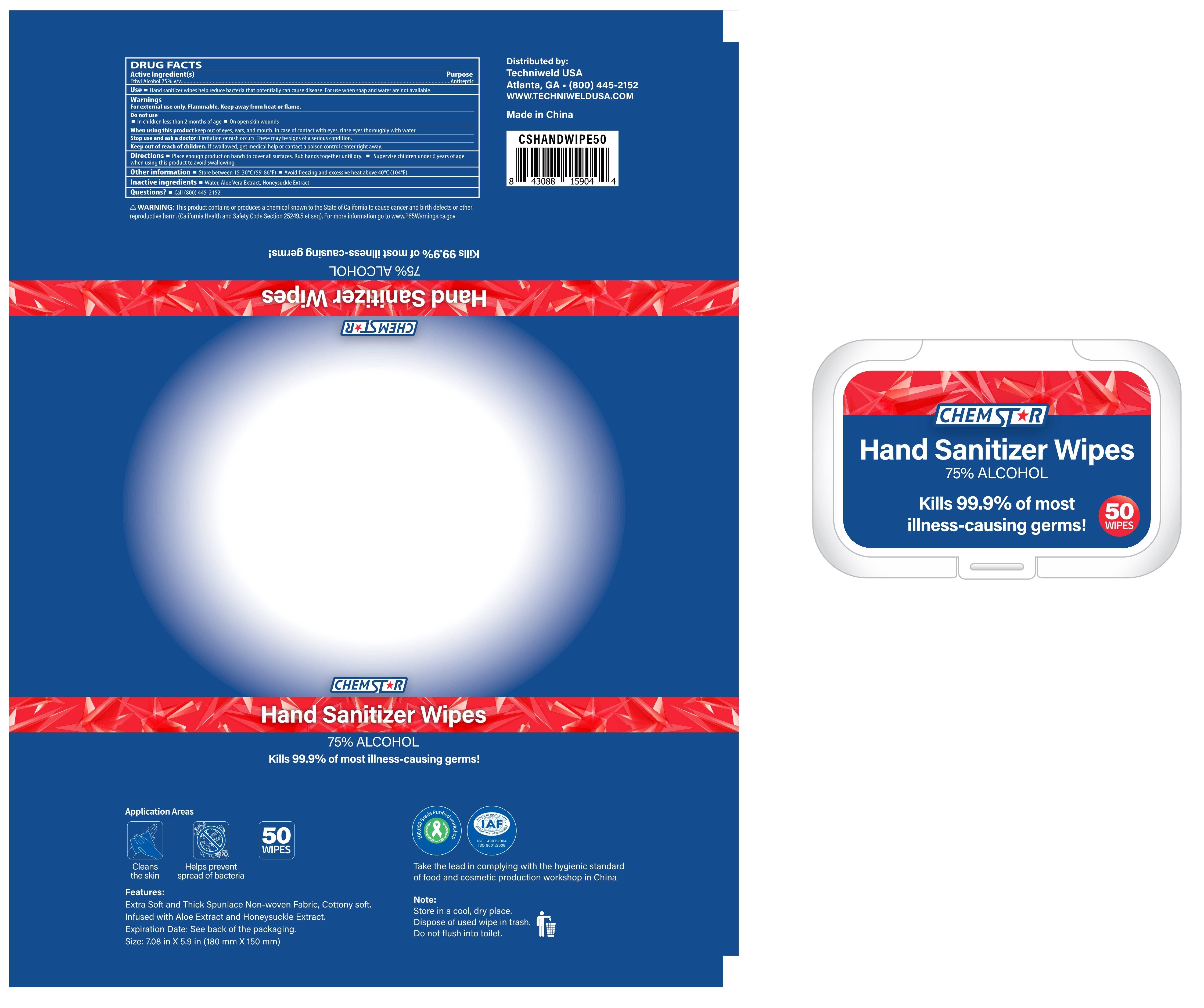 DRUG LABEL: Hand Sanitizer Wipes
NDC: 42129-015 | Form: CLOTH
Manufacturer: Fustin(Xiamen) Commodity Co., ltd
Category: otc | Type: HUMAN OTC DRUG LABEL
Date: 20200727

ACTIVE INGREDIENTS: ALCOHOL 75 1/100 1
INACTIVE INGREDIENTS: ALOE VERA LEAF; LONICERA CAPRIFOLIUM FLOWER; WATER

Hand Sanitizer Wipes

Active Ingredient(s)

Ethyl Alcohol 75% v/v

Purpose

Antiseptic

Use

Hand sanitizer wipes help reduce bacteria that potentially can cause disease. For use when soap and water are not available

Keep out of reach of children. If swallowed, get medical help or contact a poison control center right away

When using this product keep out of eyes, ears, and mouth. In case of contact with eyes, rinse eyes thoroughly with water.

Do not use

In children less than 2 months of age On open skin wounds

Stop use and ask a doctor if irritation or rash occurs. These may be signs of a serious condition

Directions

Place enough product on hands to cover all surfaces. Rub hands together until dry.
Supervise children under 6 years of age when using this product to avoid swallowing

Inactive ingredients

Water, Aloe Vera Extract, Honeysuckle Extract

STORAGE AND HANDLING

Store between 15-30°C(59-86°F)
Avoid freezing and excessive heat above 40°C(104°F)